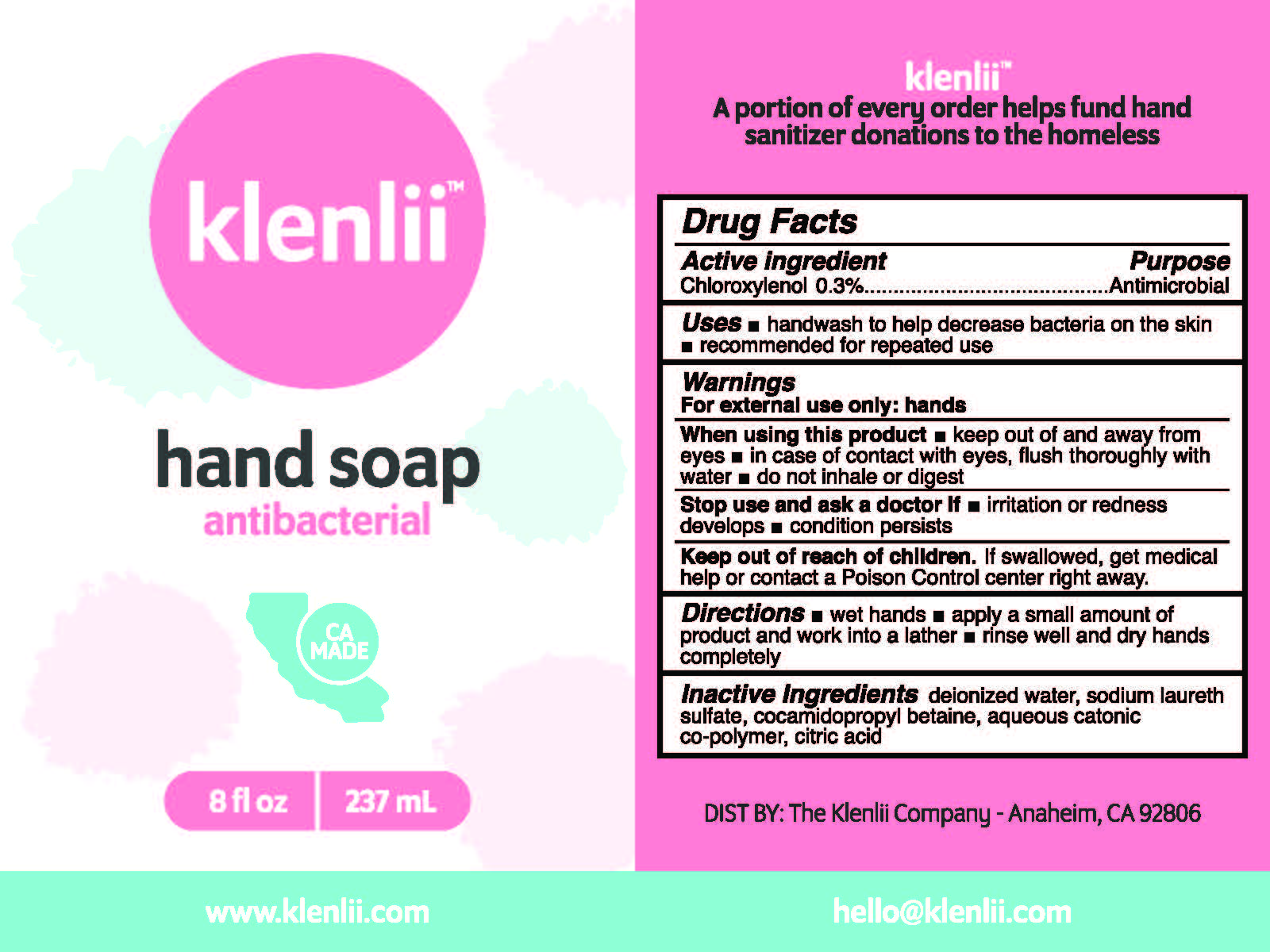 DRUG LABEL: KLENLII HAND
NDC: 78016-106 | Form: SOAP
Manufacturer: Klenlii Company
Category: otc | Type: HUMAN OTC DRUG LABEL
Date: 20240509

ACTIVE INGREDIENTS: CHLOROXYLENOL 0.3 g/100 mL
INACTIVE INGREDIENTS: WATER; SODIUM LAURETH SULFATE; COCAMIDOPROPYL BETAINE; BUTYL ACRYLATE/METHYL METHACRYLATE/METHACRYLIC ACID COPOLYMER (18000 MW); ANHYDROUS CITRIC ACID

KLENLII HAND SOAP ANTIBACTERIAL (78016-106)

ACTIVE INGREDIENT

CHLOROXYLENOL 0.3%

PURPOSE

ANTIMICROBIAL

USES

- HANDWASH TO HELP DECREASE BACTERIA ON THE SKIN
- RECOMMENDED FOR REPEATED USE

WARNINGS

FOR EXTERNAL USE ONLY: HANDS

WHEN USING THIS PRODUCT

- KEEP OUT OF AND AWAY FROM EYES
- IN CASE OF CONTACT WITH EYES, FLUSH THOROUGHLY WITH WATER
- DO NOT INHALE OR INGEST

STOP USE AND ASK DOCTOR IF

- IRRITATION OR REDNESS DEVELOPS
- CONDITION PERSISTS

KEEP OUT OF REACH OF CHILDREN. IF SWALLOWED, GET MEDICAL HELP OR CONTACT A POISON CONTROL CENTER RIGHT AWAY.

DIRECTIONS

- WET HANDS
- APPLY A SMALL AMOUNT OF PRODUCT AND WORK INTO A LATHER
- RINSE WELL AND DRY HANDS COMPLETELY

INACTIVE INGREDIENTS

DEIONIZED WATER, SODIUM LAURETH SULFATE, COCAMIDOPROPYL BETAINE, AQUEOUS CATONIC COPOLYMER, CITRIC ACID